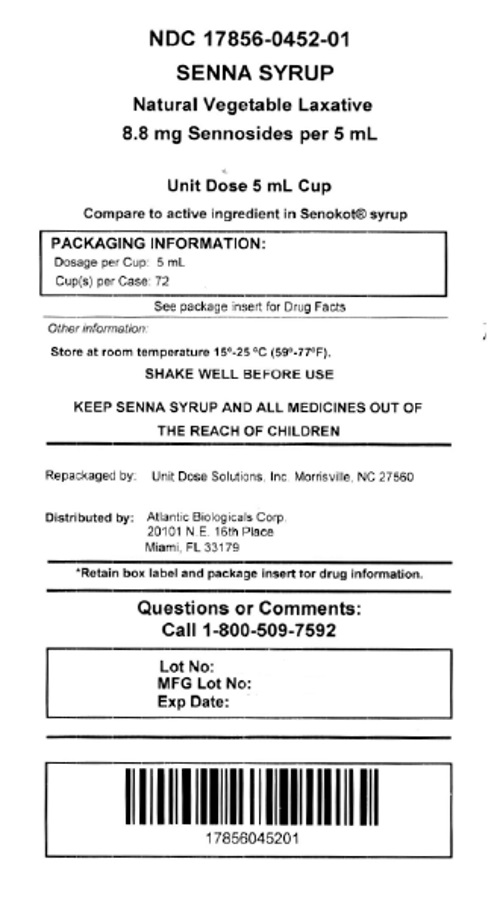 DRUG LABEL: Senna Syrup
NDC: 17856-0452 | Form: LIQUID
Manufacturer: Atlantic Biologicals Corps
Category: otc | Type: HUMAN OTC DRUG LABEL
Date: 20191018

ACTIVE INGREDIENTS: SENNOSIDES 8.8 mg/5 mL
INACTIVE INGREDIENTS: COCOA; METHYLPARABEN; CHOCOLATE HIND; PROPYLENE GLYCOL; PROPYLPARABEN; WATER; SUCROSE

Senna Syrup

ACTIVE INGREDIENT

Each 5ml Contains

Active Ingredient Purpose

Sennosides 8.8 mg .............Laxative

WARNINGS

Do not give laxative products to your child for a period longer than 1 week unless directed by a doctor

Directions

Do not exceed recomended dose
Age | Starting Dose | Maximun Dose
Adults and Children 2 years and older | 2-3 teaspoons once a day preferably at bedtime; increase as needed or as recomended by a doctor | 3 teaspoons in the morning and 3 teaspoons at bedtime
under 12 years of age | ask a doctor | ask a doctor

INDICATIONS

relieves occasional constipation (irregularity) generally causes bowel movement in 6 to 12 hours

PURPOSE

Stimulant Laxative

KEEP OUT OF REACH OF CHILDREN

In case of overdose, get medical help or contact a Poison Control center right away.

INACTIVE INGREDIENT

Ccoa Distillate Flavor, Methyparaben, Natural Chocolate Flavor, Propylene Glycol, Propylparaben, Purified Water, Sucrose